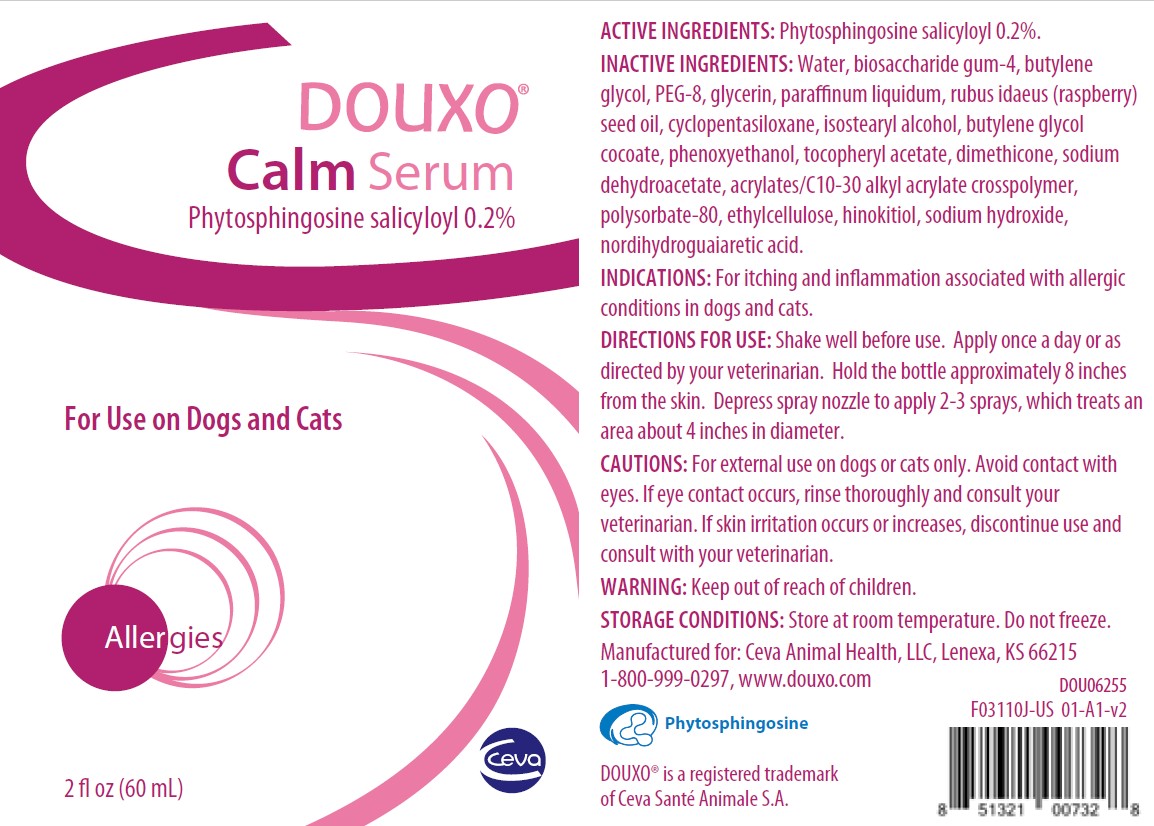 DRUG LABEL: DOUXO CALM
NDC: 13744-160 | Form: GEL
Manufacturer: Ceva Sante Animale
Category: animal | Type: OTC ANIMAL DRUG LABEL
Date: 20190430

ACTIVE INGREDIENTS: SALICYLOYL PHYTOSPHINGOSINE 0.2 mg/1 mL
INACTIVE INGREDIENTS: WATER; BIOSACCHARIDE GUM-4; BUTYLENE GLYCOL; 1,2-BUTYLENE GLYCOL MONOCOCOATE; PEG-8 DIMETHICONE; MINERAL OIL; GLYCERIN; ISOSTEARYL ALCOHOL; RASPBERRY SEED OIL; CYCLOMETHICONE 5; DIMETHICONE; ALPHA-TOCOPHEROL ACETATE; PHENOXYETHANOL; ACRYLATES/C10-30 ALKYL ACRYLATE CROSSPOLYMER (60000 MPA.S); POLYSORBATE 80; SODIUM HYDROXIDE; SODIUM DEHYDROACETATE; SODIUM HINOKITIOL; MASOPROCOL; ETHYLCELLULOSE

DOUXO CALM SERUM

DESCRIPTION

DOUXO®

Calm Serum

Phytosphingosine salicyloyl 0.2%

ACTIVE INGREDIENT: Phytosphingosine salicyloyl 0.2%

INACTIVE INGREDIENTS: Water, biosaccharide gum-4, butylene glycol, PEG-8, glycerin, paraffinum liquidum, rubus idaeus (raspberry) seed oil, cyclopentasiloxane, isostearyl alcohol, butylene glycol cocoate, phenoxyethanol, tocopheryl acetate, dimethicone, sodium dehydroacetate, acrylates/C10-30 alkyl acrylate crosspolymer, polysorbate-80, ethylcellulose, hinokitiol, sodium hydroxide, nordihydroguaiaretic acid.

INDICATIONS AND USAGE

INDICATIONS: For itching and inflammation associated with allergic conditions in dogs and cats.

DIRECTIONS FOR USE: Shake well before use. Apply once a day or as directed by your veterinarian. Hold the bottle approximately 8 inches from the skin. Depress spray nozzle to apply 2-3 sprays, which treats an area about 4 inches in diameter.

PRECAUTIONS

CAUTIONS: For external use on dogs or cats only. Avoid contact with eyes. If eye contact occurs, rinse thoroughly and consult your veterinarian. If skin irritation occurs or increases, discontinue use and consult with your veterinarian.

WARNING: Keep out of reach of children

STORAGE AND HANDLING

STORAGE CONDITIONS: Store at room temperature. Do not freeze.

Manufactured for: Ceva Animal Health, LLC, Lenexa, KS 66215

1-800-999-0297, www.douxo.com

DOUXO® is a registered trademark of Ceva Santé Animale S.A.

PRINCIPAL DISPLAY PANEL - 60 mL (2 OUNCE) Bottle

DOUXO®

Calm Serum

Phytosphingosine salicyloyl 0.2%

For Use on Dogs and Cats

Allergies

2 fl. oz. (60 mL)

Ceva